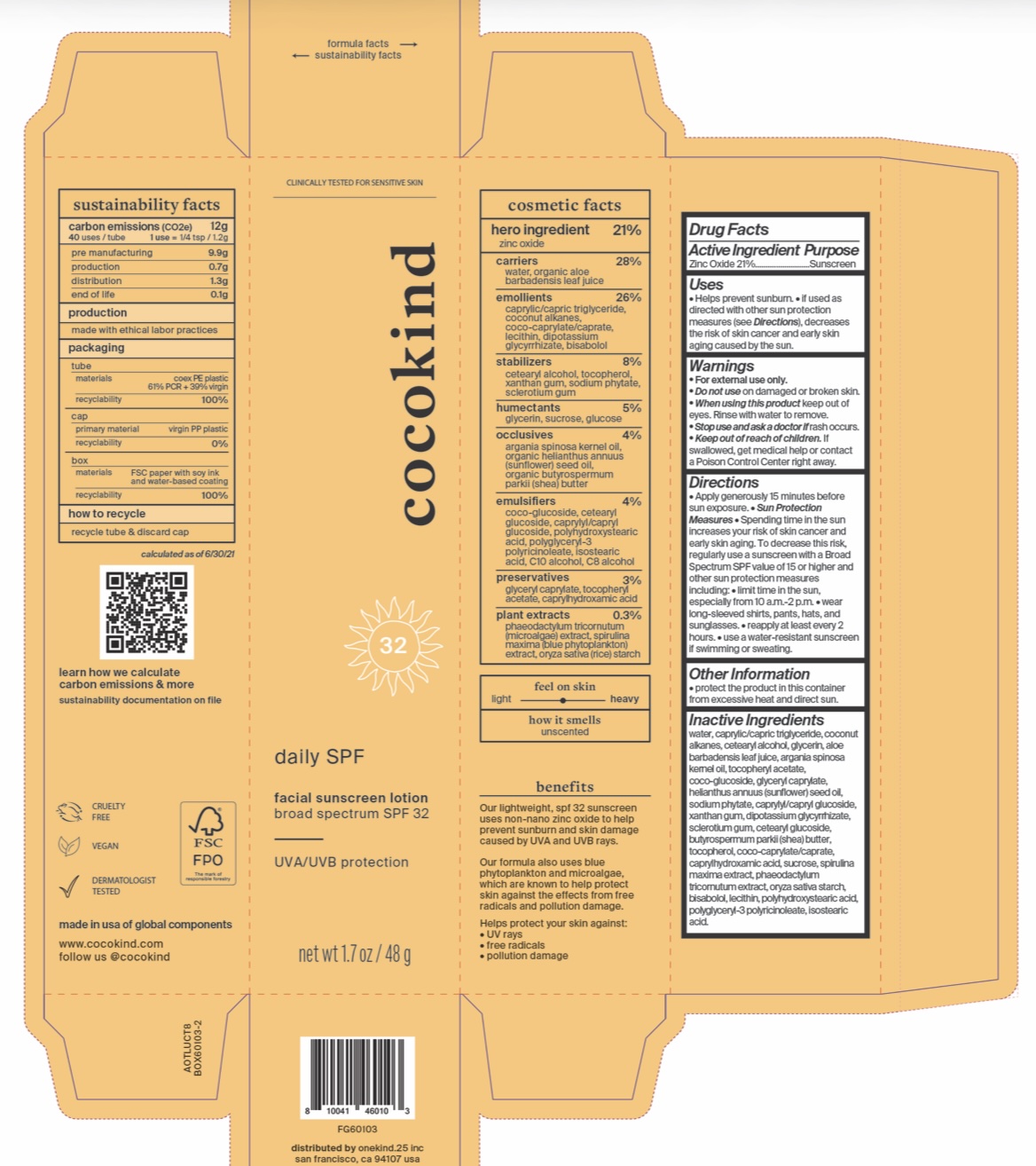 DRUG LABEL: Daily SPF Facial SunscreenLotion Broad Spectrum SPF 32
NDC: 79356-201 | Form: CREAM
Manufacturer: Onekind.25
Category: otc | Type: HUMAN OTC DRUG LABEL
Date: 20251215

ACTIVE INGREDIENTS: ZINC OXIDE 210 mg/1 g
INACTIVE INGREDIENTS: LEVOMENOL; CAPRYLHYDROXAMIC ACID; PHYTATE SODIUM; BETASIZOFIRAN; SUCROSE; PHAEODACTYLUM TRICORNUTUM; ANHYDROUS DEXTROSE; SPIRULINA MAXIMA; TOCOPHEROL; C8-10 ALCOHOLS; WATER; MEDIUM-CHAIN TRIGLYCERIDES; COCONUT ALKANES; CETOSTEARYL ALCOHOL; GLYCERIN; ALOE VERA LEAF; ARGAN OIL; .ALPHA.-TOCOPHEROL ACETATE; COCO GLUCOSIDE; SUNFLOWER OIL; GLYCERYL MONOCAPRYLATE; SHEA BUTTER; CETEARYL GLUCOSIDE; CAPRYLYL/CAPRYL OLIGOGLUCOSIDE; LECITHIN, SOYBEAN; POLYGLYCERYL-3 RICINOLEATE; POLYHYDROXYSTEARIC ACID (2300 MW); COCO-CAPRYLATE/CAPRATE; XANTHAN GUM; STARCH, RICE; ISOSTEARIC ACID; GLYCYRRHIZINATE DIPOTASSIUM

Daily SPF Facial Sunscreen Lotion Broad Spectrum SPF 32

Active Ingredients:

Zinc Oxide 21%

Purpose: Sunscreen

Uses:

- Helps prevent sunburn. If used as directed with other sun protection measures (see Direction), decreases the risk of skin cancer and early skin aging caused by the sun.

WARNINGS

Warning: For external use only.

Do not use: on damaged or broken skin.

WHEN USING

When using this products: Keep out of eyes. Rinse with water to remove.

Stop use and ask a doctor: If rash occurs.

Keep out of reach of children: If product is swallowed, get medical help or contact a Poison Control Center right away.

Directions:

Apply generously 15 minutes before sun exposer. Reapply at least every 2 hours. Use a water resistant sunscreen if swimming or sweating.

Sun protection measures: Spending time in the sun increase your risk of skin cancer and early skin aging. To decrease this risk, regularly use a sunscreen with a Broad Spectrum SPF of 15 or higher and other sun protection measures including:

- Limit time in the sun, especially from 10am - 2pm.
- Wear long sleeved shirts, pants, hats and sunglasses.

Other Information: Protect the product in this container from excessive heat and direct sun.

INACTIVE INGREDIENT

Inactive Ingredients: Water (Aqua), Caprylyc/Capric Triglyceride, Coconut Alkanes, Cetearyl Alcohol, Glycerin, Aloe Barbadensis Leaf Juice, Argania Spinosa Kernel Oil, Tocopheryl Acetate, Helianthus annuus (sunflower) seed oil, Coco-Glucoside, Glyceryl Caprylate, Butyrospermum Parkii (Shea) Butter, Cetearyl Glucoside , Xanthan Gum, Coco-Caprylate/Caprate, Lecithin, Caprylyl/Capryl Glucoside, Polyhydroxystearic Acid , Polyglyceryl-3 Polyricinoleate, Isostearic Acid, Oryza Sativa Starch, Dipotassium Glycyrrhizate, Bisabolol, Caprylhydroxamic Acid, Sodium Pthalate, Sclerotium Gum, Sucrose, Phaeodactylum Tricornutum Extract, Glucose, Spirulina Maxima Extract, Tocopherol, C10 Alochol, C8 Alcohol.